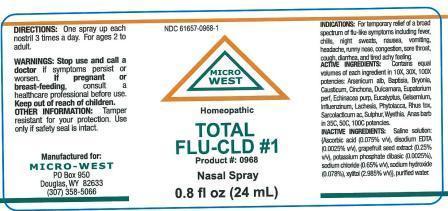 DRUG LABEL: Total FLU-CLD  1
NDC: 61657-0968 | Form: LIQUID
Manufacturer: White Manufacturing Inc. DBA Micro-West
Category: homeopathic | Type: HUMAN OTC DRUG LABEL
Date: 20140820

ACTIVE INGREDIENTS: ARSENIC TRIOXIDE 10 [hp_X]/30 mL; BAPTISIA TINCTORIA ROOT 10 [hp_X]/30 mL; BRYONIA ALBA ROOT 10 [hp_X]/30 mL; CAUSTICUM 10 [hp_X]/30 mL; CINCHONA OFFICINALIS BARK 10 [hp_X]/30 mL; SOLANUM DULCAMARA FLOWER 10 [hp_X]/30 mL; EUPATORIUM PERFOLIATUM FLOWERING TOP 10 [hp_X]/30 mL; ECHINACEA PURPUREA 10 [hp_X]/30 mL; EUCALYPTUS GLOBULUS LEAF 10 [hp_X]/30 mL; GELSEMIUM SEMPERVIRENS ROOT 10 [hp_X]/30 mL; LACHESIS MUTA VENOM 10 [hp_X]/30 mL; PHYTOLACCA AMERICANA ROOT 10 [hp_X]/30 mL; TOXICODENDRON PUBESCENS LEAF 10 [hp_X]/30 mL; LACTIC ACID, L-  10 [hp_X]/30 mL; SULFUR 10 [hp_X]/30 mL; WYETHIA HELENIOIDES ROOT 10 [hp_X]/30 mL; INFLUENZA A VIRUS 10 [hp_X]/30 mL; CAIRINA MOSCHATA HEART/LIVER AUTOLYSATE 35 [hp_C]/30 mL
INACTIVE INGREDIENTS: POTASSIUM SORBATE

DRUG FACTS

ACTIVE INGREDIENTS

Contains equal volumes of each ingredient in 10X, 30X, 100X potencies:

Arsenicum alb
Baptisia
Bryonia
Causticum
Cinchona
Dulcamara
Eupatorium perf

Echinacea purp

Eucalyptus

Gelsemium

Influenzinum

Lachesis

Phytolacca

Rhus tox

Sarcolacticum ac

Sulphur

Wyethia

Anas barb in 35C, 50C,100C potencies

PURPOSE

For a broad spectrum of flu-like symptoms including fever, chills, night sweats, nausea, vomiting, headache, runny nose, congestion, sore throat, cough, diarrhea, and tired, achy feeling

KEEP OUT OF REACH OF CHILDREN

INDICATIONS

INDICATIONS: For the temporary refief of a broad spectrum of flu-like symptoms including fever, chills, night sweats, nausea, vomiting, headache, runny nose, congestion, sore throat, cough, bronchitis, diarrhea, and tired, achy feeling

WARNINGS

WARNING: STOP USE AND CALL A DOCTOR if symptoms persist or worsen. CONTAINS ALCOHOL: in case of accidental overdose, consult a poison control center immediately

OTHER INFORMATION: Tamper resistant for your protection. Use only if safety seal is intact.

PREGNANT

IF PREGNANT OR BREAST FEEDING, consult a healthcare professional before use.

DIRECTIONS

DIRECTIONS: ONE SPRAY UP EACH NOSTRIL 3 TIMES A DAY. For ages 2 to adult

INACTIVE INGREDIENT

SALINE SOLUTION BASE

MANUFACTURE

MANUFACTURED FOR

MICRO-WEST

P. O. Box 950

DOUGLAS, WY 82633

1-307-358-5066